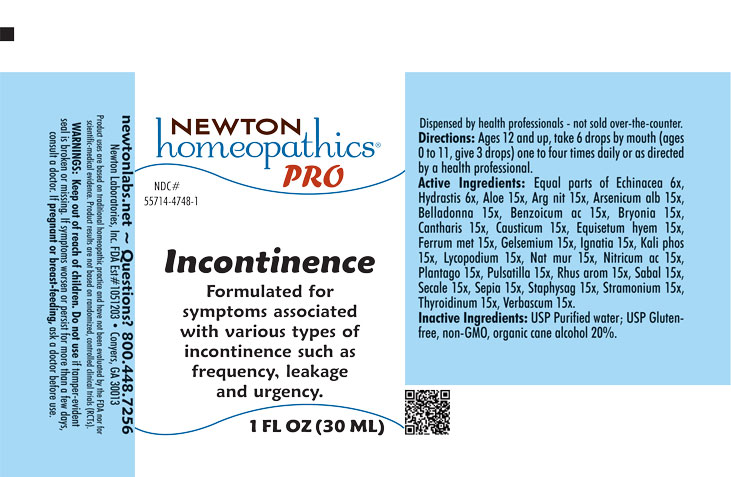 DRUG LABEL: Incontinence
NDC: 55714-4748 | Form: LIQUID
Manufacturer: Newton Laboratories, Inc.
Category: homeopathic | Type: HUMAN OTC DRUG LABEL
Date: 20250820

ACTIVE INGREDIENTS: ALOE 15 [hp_X]/1 mL; SILVER NITRATE 15 [hp_X]/1 mL; ARSENIC TRIOXIDE 15 [hp_X]/1 mL; ATROPA BELLADONNA 15 [hp_X]/1 mL; BENZOIC ACID 15 [hp_X]/1 mL; BRYONIA ALBA ROOT 15 [hp_X]/1 mL; LYTTA VESICATORIA 15 [hp_X]/1 mL; CAUSTICUM 15 [hp_X]/1 mL; EQUISETUM HYEMALE 15 [hp_X]/1 mL; IRON 15 [hp_X]/1 mL; GELSEMIUM SEMPERVIRENS ROOT 15 [hp_X]/1 mL; STRYCHNOS IGNATII SEED 15 [hp_X]/1 mL; POTASSIUM PHOSPHATE, DIBASIC 15 [hp_X]/1 mL; LYCOPODIUM CLAVATUM SPORE 15 [hp_X]/1 mL; SODIUM CHLORIDE 15 [hp_X]/1 mL; NITRIC ACID 15 [hp_X]/1 mL; PLANTAGO MAJOR 15 [hp_X]/1 mL; ANEMONE PULSATILLA 15 [hp_X]/1 mL; RHUS AROMATICA ROOT BARK 15 [hp_X]/1 mL; SAW PALMETTO 15 [hp_X]/1 mL; CLAVICEPS PURPUREA SCLEROTIUM 15 [hp_X]/1 mL; SEPIA OFFICINALIS JUICE 15 [hp_X]/1 mL; DELPHINIUM STAPHISAGRIA SEED 15 [hp_X]/1 mL; DATURA STRAMONIUM 15 [hp_X]/1 mL; THYROID, UNSPECIFIED 15 [hp_X]/1 mL; VERBASCUM THAPSUS 15 [hp_X]/1 mL; ECHINACEA, UNSPECIFIED 6 [hp_X]/1 mL; GOLDENSEAL 6 [hp_X]/1 mL
INACTIVE INGREDIENTS: ALCOHOL; WATER

Incontinence 4748L

INDICATIONS & USAGE SECTION

Formulated for symptoms associated with various types of incontinence such as frequency, leakage and urgency.

DOSAGE & ADMINISTRATION SECTION

Directions: Ages 12 and up, take 6 drops by mouth (ages 0 to 11, give 3 drops) one to four times daily or as directed by a health professional.

OTC - ACTIVE INGREDIENT SECTION

Equal parts of Echinacea 6x, Hydrastis canadensis 6x,Aloe 15x, Argentum nitricum 15x, Arsenicum album 15x, Belladonna 15x, Benzoicum acidum 15x, Bryonia 15x, Cantharis 15x, Causticum 15x, Equisetum hyemale 15x, Ferrum metallicum 15x, Gelsemium sempervirens 15x, Ignatia amara 15x, Kali phosphoricum 15x, Lycopodium clavatum 15x, Natrum muriaticum 15x, Nitricum acidum 15x, Plantago major 15x, Pulsatilla 15x, Rhus aromatica 15x, Sabal serrulata 15x, Secale cornutum 15x, Sepia 15x, Staphysagria 15x, Stramonium 15x, Thyroidinum 15x, Verbascum thapsus 15x.

OTC - PURPOSE SECTION

Formulated for symptoms associated with various types of incontinence such as frequency, leakage and urgency.

INACTIVE INGREDIENT SECTION

Inactive Ingredients: USP Purified Water; USP Gluten-free, non-GMO, organic cane alcohol 20%.

QUESTIONS SECTION

www.newtonlabs.net Newton Laboratories, Inc. FDA Est # 1051203 - Conyers, GA 30012
Questions? 1.800.448.7256

WARNINGS SECTION

WARNINGS: Keep out of reach of children. Do not use if tamper-evident seal is broken or missing. If symptoms worsen or persist for more than a few days, consult a doctor. If pregnant or breast-feeding, ask a doctor before use

OTC - PREGNANCY OR BREAST FEEDING SECTION

If pregnant or breast-feeding, ask a doctor before use

OTC - KEEP OUT OF REACH OF CHILDREN SECTION

Keep out of reach of children.